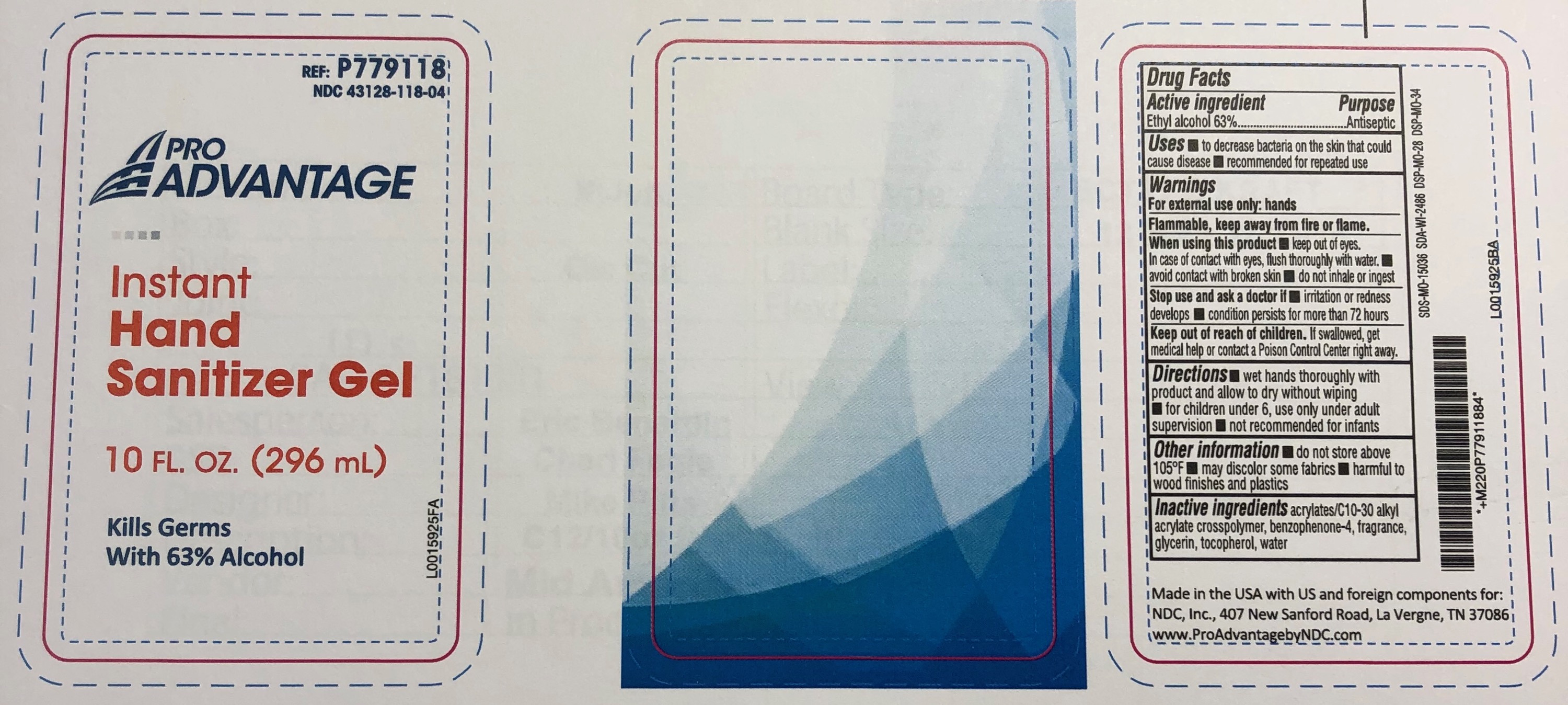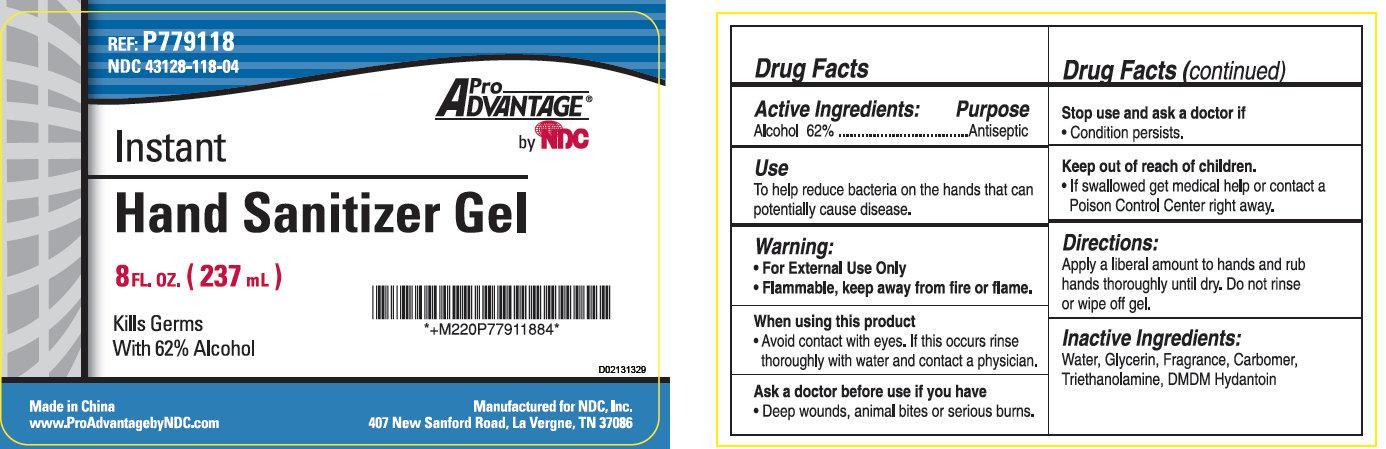 DRUG LABEL: Pro Advantage Instant Hand Sanitizer
NDC: 43128-118 | Form: GEL
Manufacturer: NDC National Distribution & Contracting, Inc.
Category: otc | Type: HUMAN OTC DRUG LABEL
Date: 20230315

ACTIVE INGREDIENTS: ALCOHOL 620 mg/1 mL
INACTIVE INGREDIENTS: WATER; GLYCERIN; TROLAMINE; DMDM HYDANTOIN

Pro Advantage Instant Hand Sanitizer Gel

Active Ingredients:

Alcohol 62%

Purpose

Antiseptic

Use

To help reduce bacteria on the hands that can potentially cause disease.

Warning:

• For External Use Only
• Flammable, keep away from fire or flame.

When using this product

• Avoid contact with eyes, if this occurs rinse thoroughly with water and contact a physician.

Ask a doctor before use if you have

• Deep wounds, animals bites or serious burns.

Stop use and ask a doctor if

• Condition persists.

Keep out of reach of children.

• If swallowed get medical help or contact a Poison Control Center right away.

Directions:

Apply a liberal amount to hands and rub hands thoroughly until dry. Do not rinse or wipe off gel.

Inactive Ingredients:

Water, Glycerin, Fragrance, Carbomer, Triethanolamine, DMDM Hydantoin

REF: P779118 NDC 43128-118-04

Made in China
www.ProAdvantagebyNDC.com
Manufactured for NDC, Inc.
407 New Sanford Road, La Vergne, TN 37086